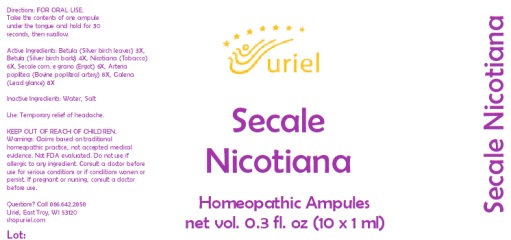 DRUG LABEL: Secale Nicotiana
NDC: 48951-8176 | Form: LIQUID
Manufacturer: Uriel Pharmacy Inc.
Category: homeopathic | Type: HUMAN OTC DRUG LABEL
Date: 20231011

ACTIVE INGREDIENTS: BETULA PUBESCENS LEAF 3 [hp_X]/1 mL; BETULA PUBESCENS BARK 4 [hp_X]/1 mL; TOBACCO LEAF 6 [hp_X]/1 mL; CLAVICEPS PURPUREA SCLEROTIUM 6 [hp_X]/1 mL; BOS TAURUS ARTERY 8 [hp_X]/1 mL; LEAD SULFIDE 8 [hp_X]/1 mL
INACTIVE INGREDIENTS: WATER; SODIUM CHLORIDE

Secale Nicotiana

INDICATIONS AND USAGE

Directions: FOR ORAL USE.

DOSAGE AND ADMINISTRATION

Take the contents of one ampule under the tongue and hold for 30 seconds, then swallow.

ACTIVE INGREDIENT

Active Ingredients: Betula (Silver birch leaves) 3X, Betula (Silver birch bark) 4X, Nicotiana (Tobacco) 6X, Secale corn. e grano (Ergot) 6X, Arteria poplitea (Bovine popliteal artery) 8X, Galena (Lead glance) 8X

Inactive Ingredients: Water, Salt

PURPOSE

Use: Temporary relief of headache.

KEEP OUT OF REACH OF CHILDREN.

WARNINGS

Warnings: Claims based on traditional homeopathic practice, not accepted medical evidence. Not FDA evaluated. Do not use if allergic to any ingredient. Consult a doctor before use for serious conditions or if conditions worsen or persist. If pregnant or nursing, consult a doctor before use.

QUESTIONS

Questions? Call 866.642.2858 Uriel, East Troy, WI 53120 shopuriel.com